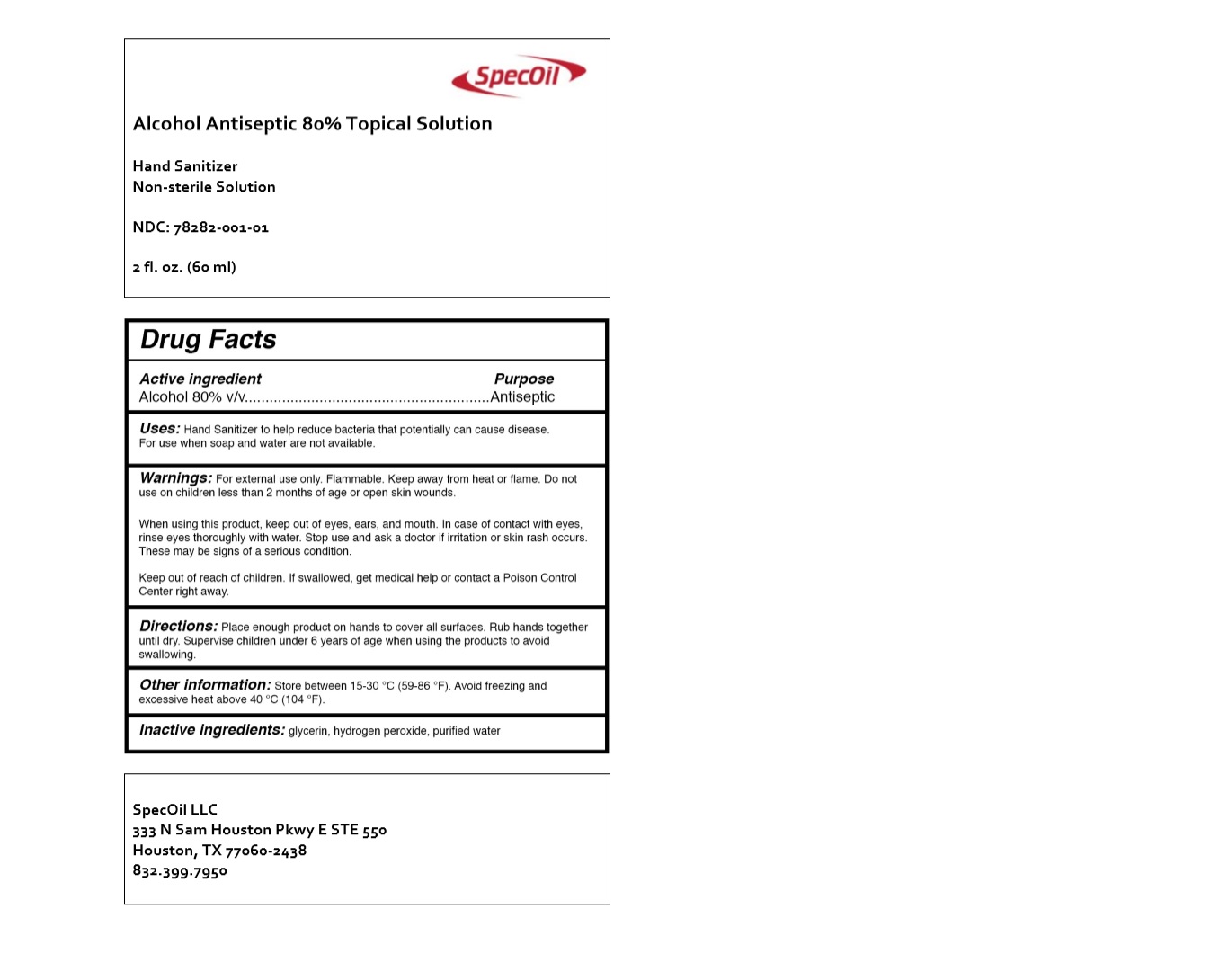 DRUG LABEL: Hand Sanitizer
NDC: 78282-001 | Form: SOLUTION
Manufacturer: Specoil, Llc
Category: otc | Type: HUMAN OTC DRUG LABEL
Date: 20200522

ACTIVE INGREDIENTS: ALCOHOL 80 mL/100 mL
INACTIVE INGREDIENTS: GLYCERIN; HYDROGEN PEROXIDE; WATER

Specoil Hand Sanitizer

Active ingredient

Alcohol 80% v/v

Purpose

Antiseptic

INDICATIONS AND USAGE

Uses: Hand Sanitizer to help reduce bacteria that potentially can cause disease. For use when soap and water are not available.

WARNINGS

Warnings: For external use only. Flammable. Keep away from heat or flame. Do not use on children less than 2 months of age

or open skin wounds.

When using this product, keep out of eyes, ears, and mouth. In case of contact with eyes, rinse eyes thoroughly with water.

Stop use and ask a doctor if irritation or skin rash occurs. These may be signs of a serious condition.

Keep out of reach of children. If swallowed, get medical help or contact a Poison Control Center right away.

DOSAGE AND ADMINISTRATION

Directions: Place enough product on hands to cover all surfaces. Rub hands together until dry.

Supervise children under 6 years of age when using this product to avoid swallowing.

Other information: Store between 15-30 ^0C (59-86 ^0F).
Avoid freezing and excessive heat above 40 ^0C (104 ^0F).

Inactive ingredients: glycerin, hydrogen peroxide, purified water

Non‐sterile Solution

SpecOil LLC

333 N Sam Houston Pkwy E STE 550

Houston, TX 77060‐2438

832.399.7950